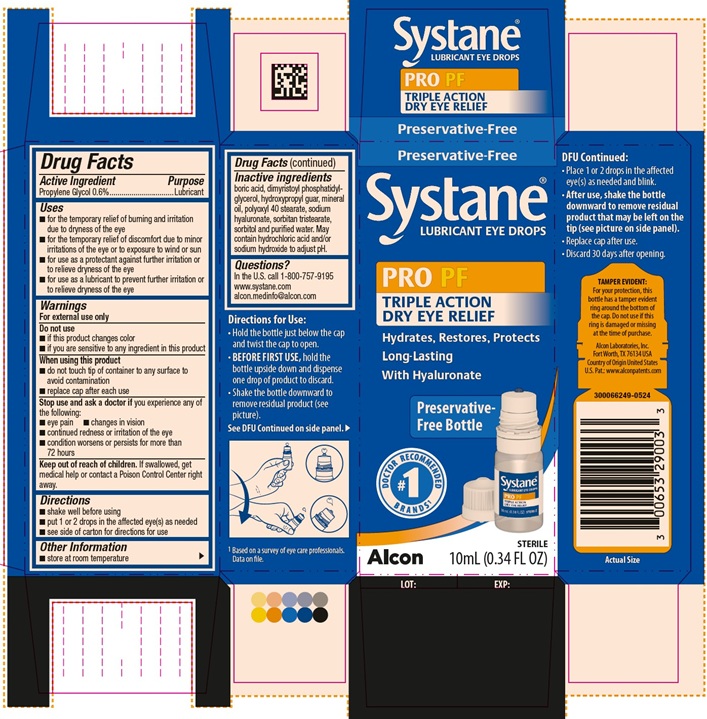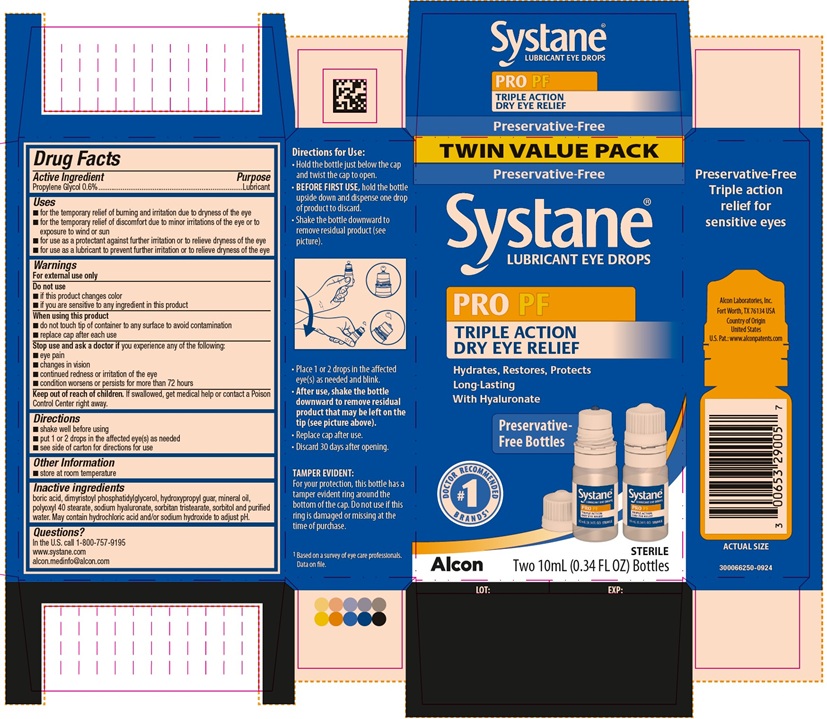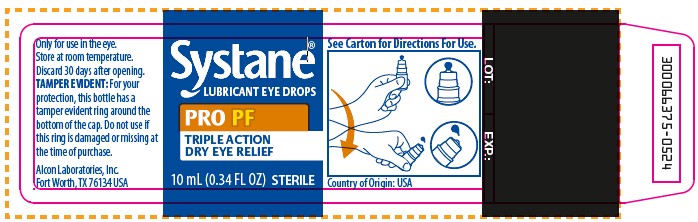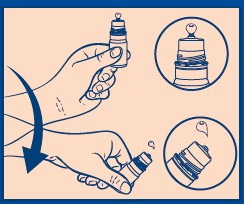 DRUG LABEL: Systane Pro PF
NDC: 0065-3290 | Form: EMULSION
Manufacturer: Alcon Laboratories, Inc.
Category: otc | Type: HUMAN OTC DRUG LABEL
Date: 20250428

ACTIVE INGREDIENTS: Propylene Glycol 6 mg/1 mL
INACTIVE INGREDIENTS: Boric Acid; Dimyristoylphosphatidylglycerol, Dl-; Guaraprolose (3500 Mpa.S At 1%); Mineral Oil; Polyoxyl 40 Stearate Type I; Hyaluronate Sodium; Sorbitan Tristearate; Sorbitol; Water; Hydrochloric Acid; Sodium Hydroxide

SYSTANE PRO PRESERVATIVE FREE
Drug Facts

ACTIVE INGREDIENT

Active Ingredients | Purpose
Propylene Glycol 0.6% | Lubricant

Uses

- for the temporary relief of burning and irritation due to dryness of the eye
- for the temporary relief of discomfort due to minor irritations of the eye or to exposure to wind or sun
- for use as a protectant against further irritation or to relieve dryness of the eye
- for use as a lubricant to prevent further irritation or to relieve dryness of the eye

Warnings

For external use only

Do not use

- if this product changes color
- if you are sensitive to any ingredient in this product

When using this product

- do not touch tip of container to any surface to avoid contamination
- replace cap after each use

Stop use and ask a doctor if you experience any of the following:

- eye pain
- changes in vision
- continued redness or irritation of the eye
- condition worsens or persists for more than 72 hours

Keep out of reach of children.

If swallowed, get medical help or contact a Poison Control Center right away.

Directions

- shake well before using
- put 1 or 2 drops in the affected eye(s) as needed
- see side of carton for directions for use

Other information

- store at room temperature

Inactive ingredients

boric acid, dimyristoyl phosphatidylglycerol, hydroxypropyl guar, mineral oil, polyoxyl 40 stearate, sodium hyaluronate, sorbitan tristearate, sorbitol and purified water. May contain hydrochloric acid and/or sodium hydroxide to adjust pH.

Questions?

In the U.S. call 1-800-757-9195
www.systane.com
alcon.medinfo@alcon.com

Directions for use:

- Hold the bottle just below the cap and twist the cap to open.
- BEFORE FIRST USE, hold the bottle upside down and dispense one drop of product to discard.
- Shake the bottle downward to remove residual product (see picture).
- Place 1 or 2 drops in the affected eye(s) as needed and blink.
- After use, shake the bottle downward to remove residual product that may be left on the tip (see picture on side panel).
- Replace cap after use.
- Discard 30 days after opening.

PRINCIPAL DISPLAY PANEL

Preservative-Free
Systane® LUBRICANT EYE DROPS
PRO PF
TRIPLE ACTION
DRY EYE RELIEF
Hydrates, Restores, Protects
Long-Lasting
With Hyaluronate
Preservative-Free Bottle
#1 DOCTOR RECOMMENDED BRANDS^1
Alcon
Sterile
10mL (0.34 FL OZ)
LOT: EXP.:
Side Panel:
TAMPER EVIDENT:
For your protection, this bottle has a tamper evident ring around the bottom of the cap. Do not
use if this ring is damaged or missing at the time of purchase.
^1Based on a survey of eye care professionals. Data on file.
Alcon Laboratories, Inc.
Fort Worth, TX 76134 USA
Country of Origin United States
U.S. Pat.: www.alconpatents.com
Actual Size
300066249-0524

PRINCIPAL DISPLAY PANEL

TWIN VALUE PACK
Preservative-Free
Systane® LUBRICANT EYE DROPS
PRO PF
TRIPLE ACTION
DRY EYE RELIEF
Hydrates, Restores, Protects
Long-Lasting
With Hyaluronate
Preservative-Free Bottles
#1 DOCTOR RECOMMENDED BRANDS^1
Alcon
Sterile
Two 10mL (0.34 FL OZ) Bottles
LOT: EXP.:
Side Panel:
TAMPER EVIDENT:
For your protection, this bottle has a tamper evident ring around the bottom of the cap. Do not use if this ring is damaged or missing at the time of purchase.
^1Based on a survey of eye care professionals. Data on file.
ACTUAL SIZE
Alcon Laboratories, Inc.
Fort Worth, TX 76134 USA
Country of Origin United States
U.S. Pat.: www.alconpatents.com
300066250-0924

PRINCIPAL DISPLAY PANEL

Systane® LUBRICANT EYE DROPS
PRO PF
TRIPLE ACTION
DRY EYE RELIEF
10mL (0.34 FL OZ)
Sterile
See Carton for Directions for Use.
Country of Origin: USA
Only for use in the eye
Store at room temperature.
Discard 30 days after opening.
TAMPER EVIDENT: For your protection, this bottle has a tamper evident ring around the bottom of the cap. Do not use if this ring is damaged or missing at the time of purchase.
Alcon Laboratories, Inc.
Fort Worth, TX 76134 USA
300066375-0524